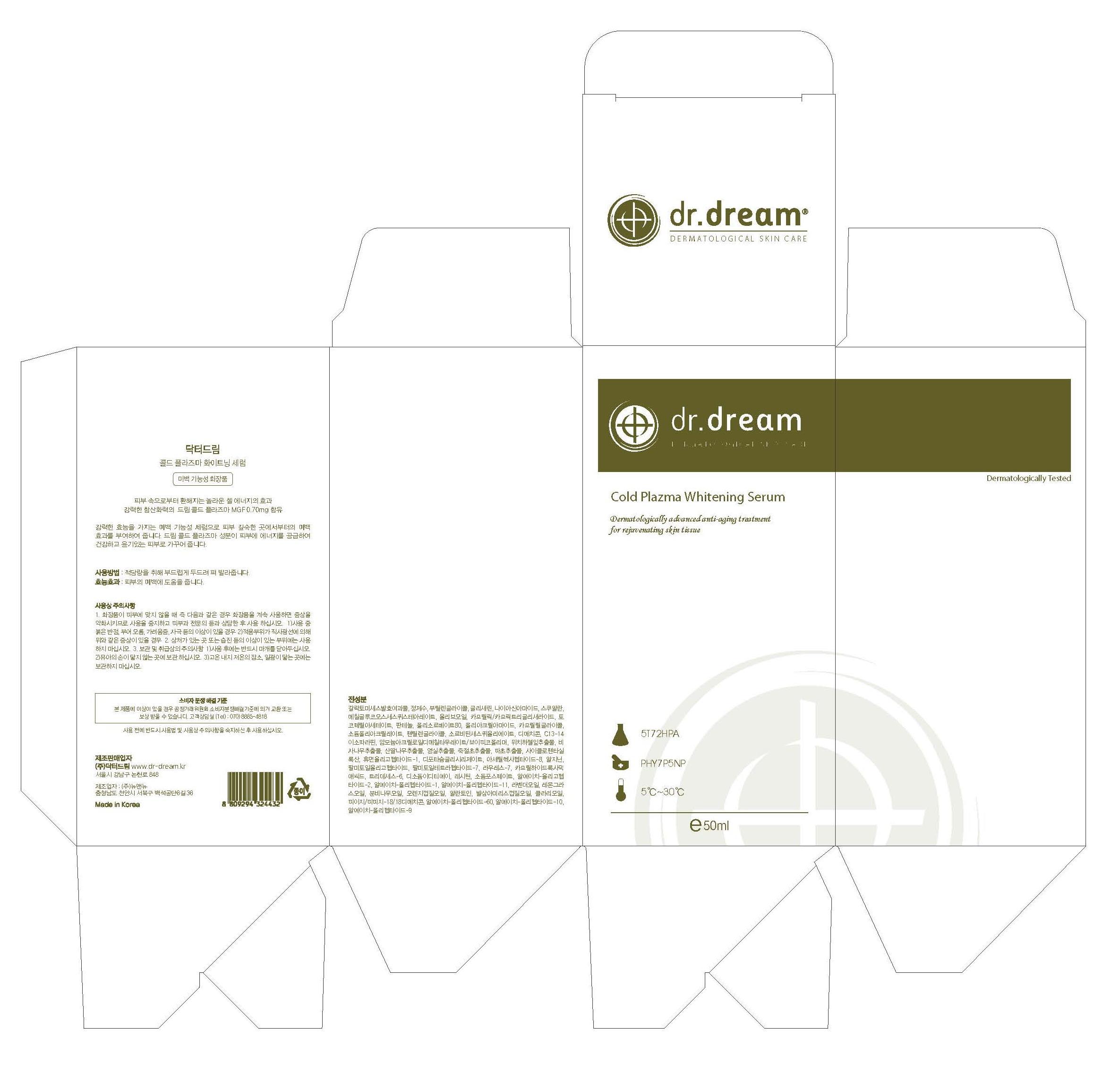 DRUG LABEL: Dr. Dream Cold Plazma Whitening Serum
NDC: 53077-7001 | Form: LIQUID
Manufacturer: Dr. Dream Inc
Category: otc | Type: HUMAN OTC DRUG LABEL
Date: 20120925

ACTIVE INGREDIENTS: WITCH HAZEL 0.1 mg/100 mL
INACTIVE INGREDIENTS: PALMITOYL OLIGOPEPTIDE; PALMITOYL TETRAPEPTIDE-7; POLYSORBATE 60; GLYCERIN; CAPRYLHYDROXAMIC ACID; ADENOSINE; AMMONIUM ACRYLOYLDIMETHYLTAURATE/VP COPOLYMER; NEOPENTYL GLYCOL; BLACK OLIVE; SODIUM CHONDROITIN SULFATE (PORCINE; 5500 MW); LAVANDULA ANGUSTIFOLIA FLOWERING TOP; CYMBOPOGON SCHOENANTHUS OIL; ABIES SIBIRICA LEAF OIL; ORANGE; AMYRIS BALSAMIFERA OIL; CLARY SAGE OIL; LECITHIN, SOYBEAN; SODIUM PHOSPHATE; HYALURONATE SODIUM; THIOREDOXIN; PREZATIDE COPPER; PALMITOYL PENTAPEPTIDE-4; GLYCINE; GLUTAMINE; LYSINE; LEUCINE; METHIONINE; VALINE; SERINE; CYSTEINE; CYSTINE; ASPARAGINE; ALANINE; ARGININE; ORNITHINE; ISOLEUCINE; TYROSINE; THREONINE; TRYPTOPHAN; PHENYLALANINE; PROLINE; HISTIDINE

Drug Facts

ACTIVE INGREDIENT

witch hazel

INACTIVE INGREDIENT

Galactomyces Ferment Filtrate, water, butylene glycol, glycerin, niacinamide, squalane, methyl glucose sesquistearate, olive fruit oil, caprylic/capric triglyceride, tocopheryl acetate, panthenol, polysorbate 80, sodium polyacrylate, caprylyl glycol, dimethicone, pentylene glycol, sorbitan sesquioleate, cyclopentasiloxane, torreya nucifera extract, cornus kousa extract, rosa mutiflora fruit extract, chloranthus glaber extract, musa basjoo extract, trideceth-6, rh-oligopeptide-1, dipotassium glycyrrhizate, acetyl hexapeptide-8, arginine, palmitoyl oligopeptide, palmitoyl tetrapeptide-7, caprylhydroxamic acid, disodium edta, lecithin, sodium phosphate, peg/ppg-18/19\8 dimethicone, rh-oligopeptide-2, rh-polypeptide-1, rh-polypeptide-11, lavender oil, cymbopogon schoenarthus oil, abies sibirica oil, orange peel oil, allantoin, amyris balsamifera bark oil, clary oil, rh-polypeptide-60, rh-polypeptide-10, rh-polypeptide-9

PURPOSE

whitening care

keep out of reach of the children

INDICATIONS AND USAGE

After applying dr. dream Advance Facial Treatment Toner, take out the proper amount and apply it to your face as massaging to be well absorbed. There would be better effect if you apply it twice a day in the morning and evening.

When using this product
- keep out of eyes, ears, and mouth. If contact occurs, rinse with plenty of cold water right away and contact a physician. If swallowing, drink plenty of water and contact a physician

DOSAGE AND ADMINISTRATION

for external use only